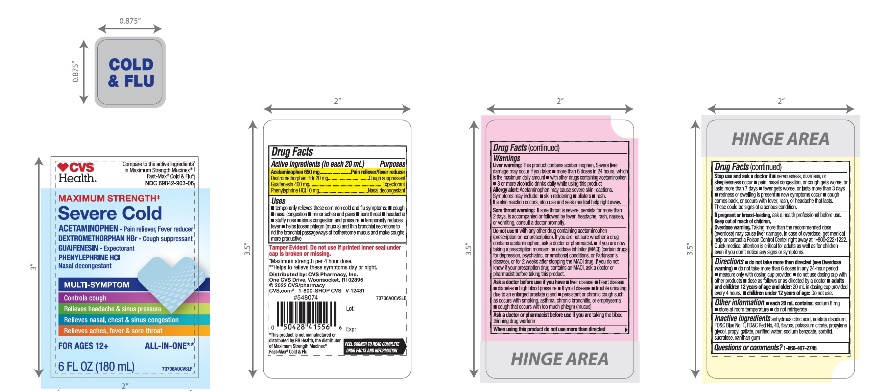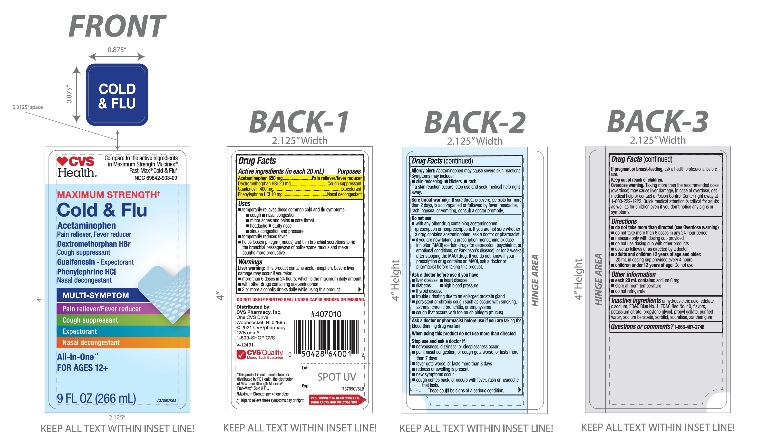 DRUG LABEL: CVS Maximum Strength Cold and Flu Relief
NDC: 69842-903 | Form: LIQUID
Manufacturer: CVS PHARMACY
Category: otc | Type: HUMAN OTC DRUG LABEL
Date: 20251210

ACTIVE INGREDIENTS: ACETAMINOPHEN 650 mg/20 mL; DEXTROMETHORPHAN HYDROBROMIDE 20 mg/20 mL; GUAIFENESIN 400 mg/20 mL; PHENYLEPHRINE HYDROCHLORIDE 10 mg/20 mL
INACTIVE INGREDIENTS: ANHYDROUS CITRIC ACID; EDETATE DISODIUM; FD&C BLUE NO. 1; FD&C RED NO. 40; POTASSIUM CITRATE; PROPYLENE GLYCOL; PROPYL GALLATE; WATER; SODIUM BENZOATE; SORBITOL; SUCRALOSE; XANTHAN GUM

CVS Maximum Strength Mucus Relief Cold, Flu and Sore Throat

Drug Facts

ACTIVE INGREDIENT

PURPOSE

Active ingredients (in each 20 mL) | Purposes
Acetaminophen 650 mg | Pain reliever/fever reducer
Dextromethorphan HBr 20 mg | Cough suppressant
Guaifenesin 400 mg | Expectorant
Phenylephrine HCl 10 mg | Nasal decongestant

Uses

- temporarily relieves these common cold and flu symptoms:
  - cough
  - nasal congestion
  - minor aches and pains
  - sore throat
  - sinus congestion and pressure
  - headache
- temporarily reduces fever
- temporarily promotes nasal and/or sinus drainage
- helps loosen phlegm (mucus) and thin bronchial secretions to rid the bronchial passageways of bothersome mucus and make coughs more productive

Warnings

Liver warning:

This product contains acetaminophen. Severe liver damage may occur if you take:

- more than 6 doses in 24 hours, which is the maximum daily amount
- with other drugs containing acetaminophen
- 3 or more alcoholic drinks daily while using this product

Generic Section

Allergy alert: Acetaminophen may cause severe skin reactions. Symptoms may include:

- skin
- blisters
- rash.

If a skin reaction occurs, stop use and seek medical help right away.

Sore throat warning:if sore throat is severe, persists for more than 2 days, is accompanied or followed by fever, headache, rash, nausea, or vomiting, consult a doctor promptly.

Do not use

- with any other drug containing acetaminophen (prescription or nonprescription). If you are not sure whether a drug contains acetaminophen, ask a doctor or pharmacist.
- for children under 12 years of age
- if you are now taking a prescription monoamine oxidase inhibitor (MAOI) (certain drugs for depression, psychiatric, or emotional conditions, or Parkinson's disease), or for 2 weeks after stopping the MAOI drug. If you do not know if your prescription drug contains an MAOI, ask a doctor or pharmacist before taking this product.

Ask a doctor before use if you have

- liver disease
- heart disease
- high blood pressure
- thyroid disease
- diabetes
- trouble urinating due to an enlarged prostate gland
- persistent or chronic cough such as occurs with smoking, asthma, chronic bronchitis, or emphysema
- cough that occurs with too much phlegm (mucus)

Ask a doctor or pharmacist before use if

- you are taking the blood thinning drug warfarin

When using this product

do not use more than directed

Stop use and ask a doctor if

- nervousness, dizziness, or sleeplessness occur
- pain, nasal congestion, or cough gets worse, or lasts more than 7 days
- fever gets worse, or lasts more than 3 days
- redness or swelling is present
- new symptoms occur
- cough comes back, or occurs with rash, or persistent headache.
- These could be signs of a serious condition.

PREGNANCY OR BREAST FEEDING

If pregnant or breast-feeding,ask a health professional before use.

Keep out of reach of children.

Overdose warning

Taking more than the recommended dose (overdose) may cause liver damage. In case of overdose, get medical help or contact a Poison Control Center right away (1-800-222-1222). Quick medical attention is critical for adults as well as for children even if you don’t notice any signs or symptoms.

Directions

- do not take more than directed (see Overdose Warning))
- do not take more than 6 doses in any 24-hour period
- measure only with dosing cup provided
- do not use dosing cup with other products
- dose as follows or as directed by a doctor
- adults and children 12 years of age and older:20 mL in dosing cup provided every 4 hours
- children under 12 years of age:Do not use

Other information

- each 20 mL contains: sodium 8 mg
- store at room temperature
- do not refrigerate

Inactive ingredients

anhydrous citric acid, edetate disodium, FD&C blue #1, FD&C red #40, flavors, potassium citrate, propylene glycol, propyl gallate, purified water, sodium benzoate, sorbitol, sucralose, xanthan gum

Questions or comments?

1-866-467-2748

Principal Display Panel

Compare to the active ingredients in Maximum Strength Mucinex® Fast-Max® Cold, Flu

NDC 69842-903-09

Maximum Strength‡

Cold, Flu &

Relief

Acetaminophen -Pain Reliever/Fever Reducer
Dextromethorphan HBr - Cough Suppressant
Guaifenesin - Expectorant
Phenylephrine HCl - Nasal Decongestant

1. ALL IN ONE*
2. Headache
3. Body Pain
4. Sore Throat
5. Fever
6. Cough
7. Chest Congestion
8. Nasal congestion
9. Sinus Congestion
10. Sinus Pressure

For Ages 12+

9FL OZ (266mL)

Principal Display Panel

NDC 69842-903-06

Maximum Strength ‡

Cold & Flu Relief

Acetaminophen -Pain Reliever/Fever Reducer
Dextromethorphan HBr - Cough Suppressant
Guaifenesin - Expectorant
Phenylephrine HCl - Nasal Decongestant

ALL IN ONE**

- Headache
- Body Pain
- Sore Throat
- Fever
- Cough
- Chest Congestion
- Nasal congestion
- Sinus Congestion
- Sinus Pressure

6 FL OZ (180 mL)

For Ages 12+

Do not use if printed seal under cap is broken or missing.

Distributed by:

*This product is not manufactured or distributed by RB Health, the distributor of Maximum Strength Mucinex® Fast-Max® Cold, Flu.

Package Label for 9 FL OZ (266 mL)